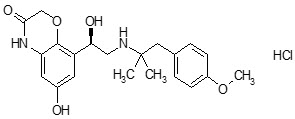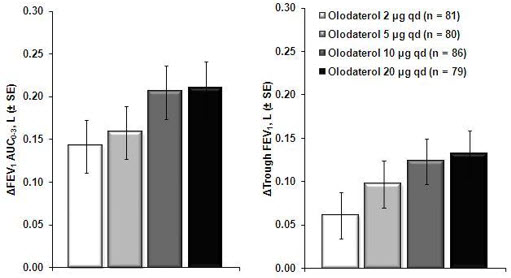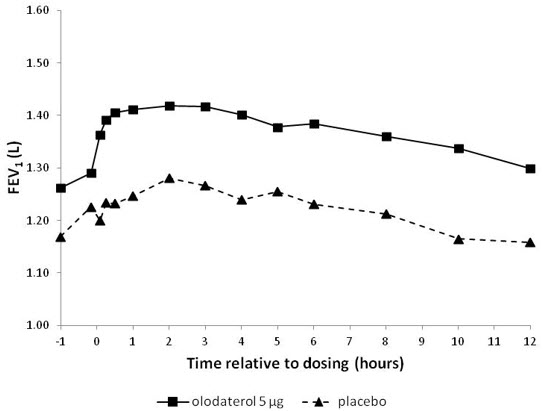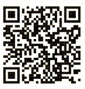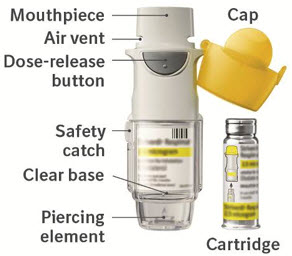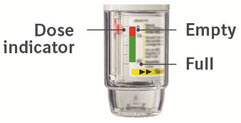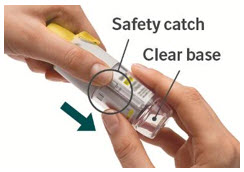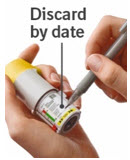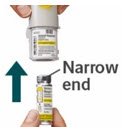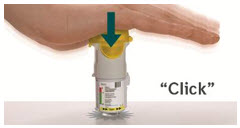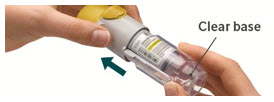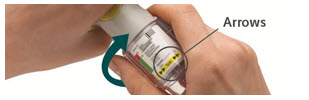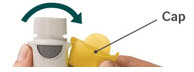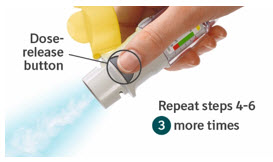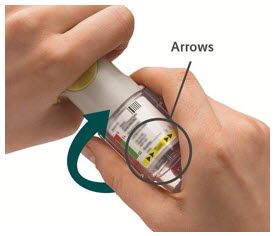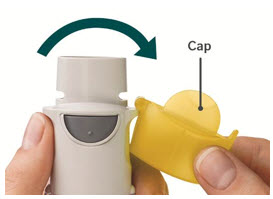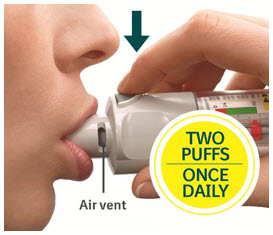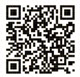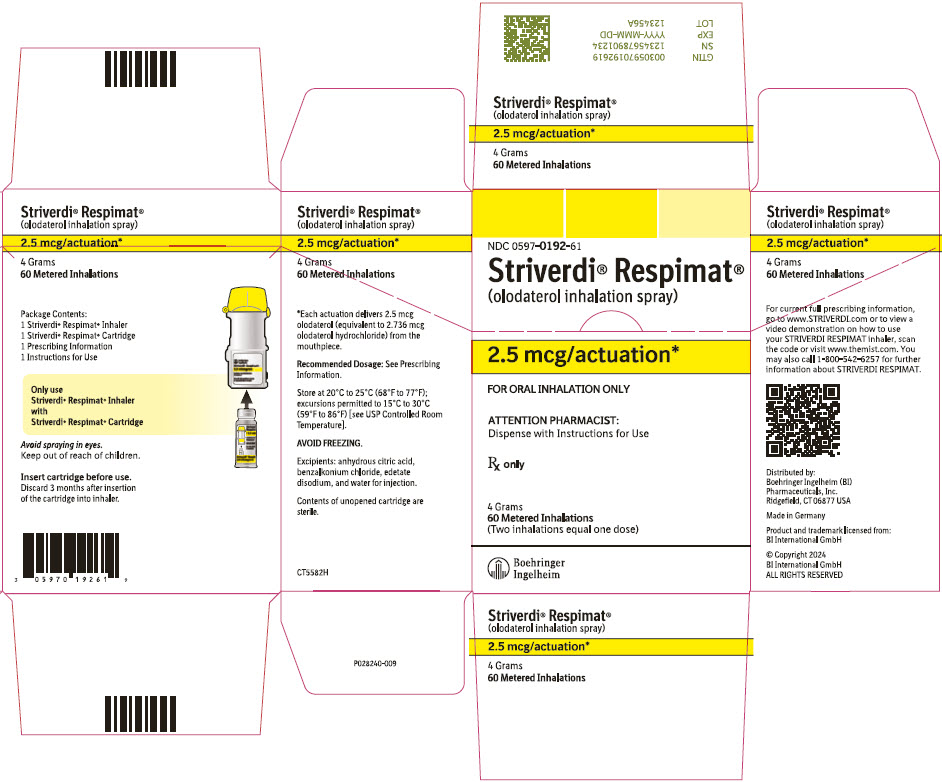 DRUG LABEL: Striverdi Respimat
NDC: 0597-0192 | Form: SPRAY, METERED
Manufacturer: Boehringer Ingelheim Pharmaceuticals, Inc.
Category: prescription | Type: HUMAN PRESCRIPTION DRUG LABEL
Date: 20250103

ACTIVE INGREDIENTS: OLODATEROL HYDROCHLORIDE 2.5 ug/1 1

HIGHLIGHTS OF PRESCRIBING INFORMATION

These highlights do not include all the information needed to use STRIVERDI RESPIMAT safely and effectively. See full prescribing information for STRIVERDI RESPIMAT.
STRIVERDI® RESPIMAT® (olodaterol inhalation spray), for oral inhalation use
Initial U.S. Approval: 2014

1 INDICATIONS AND USAGE

STRIVERDI RESPIMAT Inhalation Spray is a long-acting beta2-adrenergic agonist (LABA) indicated for:

The long-term, once-daily maintenance bronchodilator treatment of airflow obstruction in patients with chronic obstructive pulmonary disease (COPD), including chronic bronchitis and/or emphysema. (1.1)

Important limitations:

- STRIVERDI RESPIMAT is NOT indicated to treat acute deterioration of COPD. (1.2)
- STRIVERDI RESPIMAT is NOT indicated to treat asthma. (1.2)

2 DOSAGE AND ADMINISTRATION

- For oral inhalation only.
- Two inhalations of STRIVERDI RESPIMAT once-daily at the same time of day. (2)

3 DOSAGE FORMS AND STRENGTHS

Inhalation spray: Each actuation from the mouthpiece delivers 2.5 mcg olodaterol (equivalent to 2.736 mcg olodaterol hydrochloride). Two actuations equal one dose. (3)

4 CONTRAINDICATIONS

Use of a LABA, including STRIVERDI RESPIMAT, without an inhaled corticosteroid is contraindicated in patients with asthma. (4)

5 WARNINGS AND PRECAUTIONS

- LABA as monotherapy (without an inhaled corticosteroid) for asthma increases the risk of serious asthma-related events. (5.1)
- Do not initiate STRIVERDI RESPIMAT in acutely deteriorating COPD patients. (5.2)
- Do not use for relief of acute symptoms. Concomitant short-acting beta2-agonists can be used as needed for acute relief. (5.2)
- Do not exceed the recommended dosage. Excessive use of STRIVERDI RESPIMAT, or use in conjunction with other medications containing LABA can result in clinically significant cardiovascular effects and may be fatal. (5.3)
- Life-threatening paradoxical bronchospasm can occur. Discontinue STRIVERDI RESPIMAT immediately. (5.4)
- Use with caution in patients with cardiovascular or convulsive disorders, thyrotoxicosis or sensitivity to sympathomimetic drugs. (5.5, 5.6)

6 ADVERSE REACTIONS

Most common adverse reactions (incidence ≥2% and more than placebo) are nasopharyngitis, upper respiratory tract infection, bronchitis, urinary tract infection, cough, dizziness, rash, diarrhea, back pain and arthralgia. (6.1)

To report SUSPECTED ADVERSE REACTIONS, contact Boehringer Ingelheim Pharmaceuticals, Inc. at 1-800-542-6257 or FDA at 1-800-FDA-1088 or www.fda.gov/medwatch.

7 DRUG INTERACTIONS

- Other adrenergic drugs may potentiate effect. Use with caution. (5.3, 7.1)
- Xanthine derivatives, steroids, diuretics or non-potassium sparing diuretics may potentiate hypokalemia or ECG changes. Use with caution. (7.2, 7.3)
- MAO inhibitors, tricyclic antidepressants, and drugs that prolong QTc interval may potentiate effect on cardiovascular system. Use with extreme caution. (7.4)
- Beta-blockers may decrease effectiveness. Use with caution and only when medically necessary. (7.5)

FULL PRESCRIBING INFORMATION

1 INDICATIONS AND USAGE

1.1 Maintenance Treatment of COPD

STRIVERDI RESPIMAT is a long-acting beta2-agonist indicated for long-term, once-daily maintenance bronchodilator treatment of airflow obstruction in patients with chronic obstructive pulmonary disease (COPD), including chronic bronchitis and/or emphysema.

1.2 Important Limitations of Use

STRIVERDI RESPIMAT is not indicated to treat acute deteriorations of COPD [see Warnings and Precautions (5.2)].

STRIVERDI RESPIMAT is not indicated to treat asthma. The safety and effectiveness of STRIVERDI RESPIMAT in asthma have not been established.

2 DOSAGE AND ADMINISTRATION

The recommended dosage of STRIVERDI RESPIMAT is two inhalations once-daily at the same time of the day. Do not use STRIVERDI RESPIMAT more than two inhalations every 24 hours.

Prior to first use, the STRIVERDI RESPIMAT cartridge is inserted into the STRIVERDI RESPIMAT inhaler and the unit is primed. When using the unit for the first time, patients are to actuate the inhaler toward the ground until an aerosol cloud is visible and then repeat the process three more times. The unit is then considered primed and ready for use. If not used for more than 3 days, patients are to actuate the inhaler once to prepare the inhaler for use. If not used for more than 21 days, patients are to actuate the inhaler until an aerosol cloud is visible and then repeat the process three more times to prepare the inhaler for use [see Patient Counseling Information (17)].

No dosage adjustment is required for geriatric patients, patients with mild and moderate hepatic impairment, or renally-impaired patients. There are no data available for use of STRIVERDI RESPIMAT in severe hepatically impaired patients [see Clinical Pharmacology (12.3)].

3 DOSAGE FORMS AND STRENGTHS

STRIVERDI RESPIMAT consists of a STRIVERDI RESPIMAT inhaler and an aluminum cylinder (STRIVERDI RESPIMAT cartridge) containing olodaterol (as the hydrochloride). The STRIVERDI RESPIMAT cartridge is intended for use with the STRIVERDI RESPIMAT inhaler only.

Each actuation from the STRIVERDI RESPIMAT inhaler delivers 2.5 mcg olodaterol (equivalent to 2.736 mcg olodaterol hydrochloride) from the mouthpiece. Two actuations equal one dose.

4 CONTRAINDICATIONS

Use of a LABA, including STRIVERDI RESPIMAT, without an inhaled corticosteroid is contraindicated in patients with asthma [see Warnings and Precautions (5.1)]. STRIVERDI RESPIMAT is not indicated for the treatment of asthma.

5 WARNINGS AND PRECAUTIONS

5.1 Serious Asthma-Related Events – Hospitalizations, Intubations, Death

- The safety and efficacy of STRIVERDI RESPIMAT in patients with asthma have not been established. STRIVERDI RESPIMAT is not indicated for the treatment of asthma [see Contraindications (4)].
- Use of long-acting beta2-adrenergic agonists (LABA) as monotherapy [without inhaled corticosteroids (ICS)] for asthma is associated with an increased risk of asthma-related death. Available data from controlled clinical trials also suggest that use of LABA as monotherapy increases the risk of asthma-related hospitalization in pediatric and adolescent patients. These findings are considered a class effect of LABA monotherapy. When LABA are used in fixed-dose combination with ICS, data from large clinical trials do not show a significant increase in the risk of serious asthma-related events (hospitalizations, intubations, death) compared with ICS alone.
- A 28-week, placebo-controlled US study comparing the safety of another LABA (salmeterol) with placebo, each added to usual asthma therapy, showed an increase in asthma-related deaths in patients receiving salmeterol (13/13,176 in patients treated with salmeterol vs. 3/13,179 in patients treated with placebo; RR 4.37, 95% CI 1.25, 15.34). The increased risk of asthma-related death is considered a class effect of LABA, including STRIVERDI RESPIMAT.
- No study adequate to determine whether the rate of asthma-related death is increased in patients treated with STRIVERDI RESPIMAT has been conducted.
- Available data do not suggest an increased risk of death with use of LABA in patients with COPD.

5.2 Deterioration of Disease and Acute Episodes

STRIVERDI RESPIMAT should not be initiated in patients with acutely deteriorating COPD, which may be a life-threatening condition. STRIVERDI RESPIMAT has not been studied in patients with acutely deteriorating COPD. The use of STRIVERDI RESPIMAT in this setting is inappropriate.

STRIVERDI RESPIMAT should not be used for the relief of acute symptoms, i.e., as rescue therapy for the treatment of acute episodes of bronchospasm. STRIVERDI RESPIMAT has not been studied in the relief of acute symptoms and extra doses should not be used for that purpose. Acute symptoms should be treated with an inhaled short-acting beta2-agonist.

When beginning STRIVERDI RESPIMAT, patients who have been taking inhaled, short-acting beta2-agonists on a regular basis (e.g., four times a day) should be instructed to discontinue the regular use of these drugs and use them only for symptomatic relief of acute respiratory symptoms. When prescribing STRIVERDI RESPIMAT, the healthcare provider should also prescribe an inhaled, short-acting beta2-agonist and instruct the patient on how it should be used. Increasing inhaled beta2-agonist use is a signal of deteriorating disease for which prompt medical attention is indicated.

COPD may deteriorate acutely over a period of hours or chronically over several days or longer. If STRIVERDI RESPIMAT no longer controls symptoms of bronchoconstriction, or the patient's inhaled, short-acting beta2-agonist becomes less effective or the patient needs more inhalation of short-acting beta2-agonist than usual, these may be markers of deterioration of disease. In this setting, a re-evaluation of the patient and the COPD treatment regimen should be undertaken at once. Increasing the daily dosage of STRIVERDI RESPIMAT beyond the recommended dosage is not appropriate in this situation.

5.3 Excessive Use of STRIVERDI RESPIMAT and Use with Long-Acting Beta2-Agonists

As with other inhaled drugs containing beta2-adrenergic agents, STRIVERDI RESPIMAT should not be used more often than recommended, at higher doses than recommended, or in conjunction with other medications containing long-acting beta2-agonists, as an overdose may result. Clinically significant cardiovascular effects and fatalities have been reported in association with excessive use of inhaled sympathomimetic drugs.

5.4 Paradoxical Bronchospasm

As with other inhaled beta2-agonists, STRIVERDI RESPIMAT may produce paradoxical bronchospasm that may be life-threatening. If paradoxical bronchospasm occurs, STRIVERDI RESPIMAT should be discontinued immediately and alternative therapy instituted.

5.5 Cardiovascular Effects

STRIVERDI RESPIMAT, like other beta2-agonists, can produce a clinically significant cardiovascular effect in some patients as measured by increases in pulse rate, systolic or diastolic blood pressure, and/or symptoms. If such effects occur, STRIVERDI RESPIMAT may need to be discontinued. In addition, beta-agonists have been reported to produce ECG changes, such as flattening of the T wave, prolongation of the QTc interval, and ST segment depression. The clinical significance of these findings is unknown. Long acting beta2-adrenergic agonists should be administered with caution in patients with cardiovascular disorders, especially coronary insufficiency, cardiac arrhythmias, hypertrophic obstructive cardiomyopathy, and hypertension.

5.6 Co-existing Conditions

STRIVERDI RESPIMAT, like other sympathomimetic amines, should be used with caution in patients with convulsive disorders or thyrotoxicosis, in patients with known or suspected prolongation of the QT interval, and in patients who are unusually responsive to sympathomimetic amines. Doses of the related beta2-agonist albuterol, when administered intravenously, have been reported to aggravate pre-existing diabetes mellitus and ketoacidosis.

5.7 Hypokalemia and Hyperglycemia

Beta-adrenergic agonists may produce significant hypokalemia in some patients, which has the potential to produce adverse cardiovascular effects [see Clinical Pharmacology (12.2)]. The decrease in serum potassium is usually transient, not requiring supplementation. Inhalation of high doses of beta2-adrenergic agonists may produce increases in plasma glucose.

In patients with severe COPD, hypokalemia may be potentiated by hypoxia and concomitant treatment [see Drug Interactions (7.2)], which may increase the susceptibility for cardiac arrhythmias.

Clinically notable decreases in serum potassium or changes in blood glucose were infrequent during clinical studies with long-term administration of STRIVERDI RESPIMAT with the rates similar to those for placebo controls. STRIVERDI RESPIMAT has not been investigated in patients whose diabetes mellitus is not well controlled.

5.8 Hypersensitivity Reactions

Immediate hypersensitivity reactions, including angioedema, may occur after administration of STRIVERDI RESPIMAT. If such a reaction occurs, therapy with STRIVERDI RESPIMAT should be stopped at once and alternative treatment should be considered.

6 ADVERSE REACTIONS

Long-acting beta2-adrenergic agonists, such as STRIVERDI RESPIMAT, as monotherapy (without an inhaled corticosteroid) for asthma, increase the risk of asthma-related events. STRIVERDI RESPIMAT is not indicated for the treatment of asthma [see Warnings and Precautions (5.1)].

6.1 Clinical Trials Experience in Chronic Obstructive Pulmonary Disease

Because clinical trials are conducted under widely varying conditions, adverse reaction rates observed in the clinical trials of a drug cannot be directly compared with rates in the clinical trials of another drug and may not reflect the rates observed in practice.

The STRIVERDI RESPIMAT clinical development program included seven dose-ranging trials and eight confirmatory trials. Four of the confirmatory trials were 6-week cross-over trials and four were 48-week parallel group trials. Adverse reactions observed in the dose-ranging trials and four 6-week cross-over trials were consistent with those observed in the 48-week parallel group trials, which formed the primary safety database.

The primary safety database consisted of pooled data from the four 48-week double-blind, active and placebo-controlled, parallel group confirmatory clinical trials. These trials included 3,104 adult COPD patients (77% males and 23% females) 40 years of age and older. Of these patients, 876 and 883 patients were treated with STRIVERDI RESPIMAT 5 mcg and 10 mcg once-daily, respectively. The STRIVERDI RESPIMAT groups were composed of mostly Caucasians (66%) with a mean age of 64 years and a mean percent predicted FEV1 at baseline of 44% for both the 5 mcg and 10 mcg treatment groups. Control arms for comparison included placebo in all four trials plus formoterol 12 mcg in two trials.

In these four clinical trials, seventy-two percent (72%) of patients exposed to any dose of STRIVERDI RESPIMAT reported an adverse reaction compared to 71% in the placebo group. The proportion of patients who discontinued due to an adverse reaction was 7.2% for STRIVERDI RESPIMAT treated patients compared to 8.8% for placebo treated patients. The adverse reaction most commonly leading to discontinuation was worsening COPD. The most common serious adverse reactions were COPD exacerbation, pneumonia, and atrial fibrillation.

Table 1 shows all adverse drug reactions reported by at least 2% of patients (and higher than placebo) who received STRIVERDI RESPIMAT 5 mcg during the 48-week trials.

Table 1 Number and frequency of adverse drug reactions greater than 2% (and higher than placebo) in COPD patients exposed to STRIVERDI RESPIMAT 5 mcg: Pooled data from the four 48-week, double-blind, active- and placebo-controlled clinical trials in COPD patients 40 years of age and older
Treatment | STRIVERDI 5 mcg once-daily | Placebo
Body system (adverse drug reaction) | n=876 n (%) | n=885 n (%)
Infections and infestations
Nasopharyngitis | 99 (11.3) | 68 (7.7)
Upper Respiratory Tract Infection | 72 (8.2) | 66 (7.5)
Bronchitis | 41 (4.7) | 32 (3.6)
Urinary Tract Infection | 22 (2.5) | 9 (1.0)
Respiratory, thoracic, and mediastinal disorders
Cough | 37 (4.2) | 35 (4.0)
Nervous system disorders
Dizziness | 20 (2.3) | 19 (2.1)
Skin and subcutaneous tissue disorders
Rash* | 19 (2.2) | 10 (1.1)
Gastrointestinal disorders
Diarrhea | 25 (2.9) | 22 (2.5)
Musculoskeletal and connective tissue disorders
Back Pain | 31 (3.5) | 24 (2.7)
Arthralgia | 18 (2.1) | 7 (0.8)
*Rash includes a grouping of similar terms

Additional adverse reactions that occurred in greater than 2% (and higher than placebo) of patients exposed to STRIVERDI RESPIMAT 10 mcg were pneumonia, constipation, and pyrexia.

Lung cancers were reported in 6 (0.7%), 3 (0.3%), and 2 (0.2%) patients who received STRIVERDI RESPIMAT 10 mcg, 5 mcg, and placebo, respectively.

7 DRUG INTERACTIONS

7.1 Adrenergic Drugs

If additional adrenergic drugs are to be administered by any route, they should be used with caution because the sympathetic effects of STRIVERDI RESPIMAT may be potentiated [see Warnings and Precautions (5.3, 5.5, 5.6, 5.7)].

7.2 Xanthine Derivatives, Steroids, or Diuretics

Concomitant treatment with xanthine derivatives, steroids, or diuretics may potentiate any hypokalemic effect of STRIVERDI RESPIMAT [see Warnings and Precautions (5.7)].

7.3 Non-Potassium Sparing Diuretics

The ECG changes and/or hypokalemia that may result from the administration of non-potassium sparing diuretics (such as loop or thiazide diuretics) can be acutely worsened by beta-agonists, especially when the recommended dosage of the beta-agonist is exceeded. Although the clinical significance of these effects is not known, caution is advised in the co-administration of beta-agonists with non-potassium-sparing diuretics.

7.4 Monoamine Oxidase Inhibitors, Tricyclic Antidepressants, QTc Prolonging Drugs

STRIVERDI RESPIMAT, as with other beta2-agonists, should be administered with extreme caution to patients being treated with monoamine oxidase inhibitors or tricyclic antidepressants or other drugs known to prolong the QTc interval because the action of adrenergic agonists on the cardiovascular system may be potentiated by these agents. Drugs that are known to prolong the QTc interval may be associated with an increased risk of ventricular arrhythmias.

7.5 Beta-Blockers

Beta-adrenergic receptor antagonists (beta-blockers) and STRIVERDI RESPIMAT may interfere with the effect of each other when administered concurrently. Beta-blockers not only block the therapeutic effects of beta-agonists, but may produce severe bronchospasm in COPD patients. Therefore, patients with COPD should not normally be treated with beta-blockers. However, under certain circumstances, e.g. as prophylaxis after myocardial infarction, there may be no acceptable alternatives to the use of beta-blockers in patients with COPD. In this setting, cardioselective beta-blockers could be considered, although they should be administered with caution.

7.6 Inhibitors of Cytochrome P450 and P-gp Efflux Transporter

In a drug interaction study using the strong dual CYP and P-gp inhibitor ketoconazole, a 1.7-fold increase of maximum plasma concentrations and AUC was observed [see Clinical Pharmacology (12.3)]. STRIVERDI RESPIMAT was evaluated in clinical trials for up to one year at doses up to twice the recommended therapeutic dosage. No dosage adjustment is necessary.

8 USE IN SPECIFIC POPULATIONS

8.1 Pregnancy

Risk Summary

There are no adequate and well-controlled clinical studies with STRIVERDI RESPIMAT in pregnant women to inform of drug-associated risk of adverse pregnancy-related outcomes. There are clinical considerations with the use of STRIVERDI RESPIMAT in pregnant women (see Clinical Considerations). Based on animal studies, olodaterol was not teratogenic when administered to pregnant rats or rabbits during organogenesis at inhalation doses of approximately 2,731 or 1,353 times the maximum recommended human daily inhalation dose (MRHDID) (on an AUC basis) in rats or rabbits, respectively (see Data).

The estimated background risk of major birth defects and miscarriage for the indicated population is unknown. All pregnancies have a background risk of birth defect, loss or other adverse outcomes. In the U.S. general population, the estimated background risk of major birth defects and miscarriage in clinically recognized pregnancies is 2% to 4% and 15% to 20%, respectively.

Clinical Considerations

Labor and Delivery

There are no adequate and well-controlled human studies that have investigated the effects of STRIVERDI RESPIMAT during labor and delivery. Because of the potential for beta-agonist interference with uterine contractility, use of STRIVERDI RESPIMAT during labor should be restricted to those patients in whom the benefits clearly outweigh the risks.

Data

Animal Data

STRIVERDI RESPIMAT was not teratogenic in rats at inhalation doses approximately 2,731 times the MRHDID (on an AUC basis at a maternal inhalation dose of 1,054 mcg/kg/day). No significant effects occurred in rabbits at inhalation doses approximately 1,353 times the MRHDID in adults (on an AUC basis at a maternal inhalation dose of 974 mcg/kg/day). Placental transfer of olodaterol was observed in pregnant rats.

Olodaterol has been shown to be teratogenic in New Zealand rabbits at inhalation doses approximately 7,130 times the MRHDID in adults (on an AUC basis at a maternal inhalation dose of 2,489 mcg/kg/day). STRIVERDI RESPIMAT exhibited the following fetal toxicities: enlarged or small heart atria or ventricles, eye abnormalities, and split or distorted sternum.

8.2 Lactation

Risk Summary

There are no available data on the presence of olodaterol in human milk, the effects on the breastfed infant, or the effects on milk production. Olodaterol, the active component of STRIVERDI RESPIMAT, and/or its metabolites are present in the milk of lactating rats, however, due to species-specific differences in lactation physiology, the clinical relevance of these data are not clear (see Data). The developmental and health benefits of breastfeeding should be considered along with the mother's clinical need for STRIVERDI RESPIMAT and any potential adverse effects on the breastfed child from STRIVERDI RESPIMAT or from the underlying maternal condition.

Data

The distribution of olodaterol into milk was investigated after a single intravenous administration of 0.4 μmol/kg to lactating rats. Olodaterol and/or its metabolites are present in the milk of lactating rats at concentrations above those in plasma.

8.4 Pediatric Use

STRIVERDI RESPIMAT is not indicated for use in children. The safety and effectiveness of STRIVERDI RESPIMAT in the pediatric population have not been established.

8.5 Geriatric Use

Based on available data, no adjustment of STRIVERDI RESPIMAT dosage in geriatric patients is necessary.

Of the 876 patients who received STRIVERDI RESPIMAT at the recommended dose of 5 mcg once-daily in the clinical studies from the pooled 1-year database, 485 were less than or equal to 65 years of age and 391 (44.6%) were greater than 65 years of age.

No overall differences in effectiveness were observed, and in the 1-year pooled data, the adverse drug reaction profiles were similar in the older population compared to the patient population overall.

8.6 Hepatic Impairment

Subjects with mild and moderate hepatic impairment showed no changes in Cmax or AUC, nor did protein binding differ between mild and moderate hepatically impaired subjects and their healthy controls. A study in subjects with severe hepatic impairment was not performed.

8.7 Renal Impairment

Subjects with severe renal impairment showed no clinically relevant changes in Cmax or AUC compared to their healthy controls.

10 OVERDOSAGE

The expected signs and symptoms with overdosage of STRIVERDI RESPIMAT are those of excessive beta-adrenergic stimulation and occurrence or exaggeration of any of the signs and symptoms, e.g., myocardial ischemia, angina pectoris, hypertension or hypotension, tachycardia, arrhythmias, palpitations, dizziness, nervousness, insomnia, anxiety, headache, tremor, dry mouth, muscle spasms, nausea, fatigue, malaise, hypokalemia, hyperglycemia, and metabolic acidosis. As with all inhaled sympathomimetic medications, cardiac arrest and even death may be associated with an overdose of STRIVERDI RESPIMAT.

Treatment of overdosage consists of discontinuation of STRIVERDI RESPIMAT together with institution of appropriate symptomatic and supportive therapy. The judicious use of a cardioselective beta-receptor blocker may be considered, bearing in mind that such medication can produce bronchospasm. There is insufficient evidence to determine if dialysis is beneficial for overdosage of STRIVERDI RESPIMAT. Cardiac monitoring is recommended in cases of overdosage.

11 DESCRIPTION

The active moiety olodaterol is a selective beta2-adrenergic bronchodilator. The drug substance, olodaterol hydrochloride, is chemically described as 2H-1,4-Benzoxazin-3H(4H)-one, 6-hydroxy-8-[(1R)-1-hydroxy-2-[[2-(4-methoxyphenyl)-1,1-dimethylethyl]-amino]ethyl]-, monohydrochloride. Olodaterol hydrochloride is a white to off-white powder that is sparingly-slightly soluble in water and slightly soluble in ethanol. The molecular weight is 422.9 g/mole (salt): 386.5 g/mole (base), and the molecular formula is C21H26N2O5 × HCl as a hydrochloride. The conversion factor from salt to free base is 1.094.

The structural formula is:

The drug product, STRIVERDI RESPIMAT, is composed of a sterile, aqueous solution of olodaterol hydrochloride filled into a 4.5 mL plastic container crimped into an aluminum cylinder (STRIVERDI RESPIMAT cartridge) for use with the STRIVERDI RESPIMAT inhaler.

Excipients include anhydrous citric acid, benzalkonium chloride, edetate disodium, and water for injection. The STRIVERDI RESPIMAT cartridge is only intended for use with the STRIVERDI RESPIMAT inhaler. The STRIVERDI RESPIMAT inhaler is a hand held, pocket sized oral inhalation device that uses mechanical energy to generate a slow-moving aerosol cloud of medication from a metered volume of the drug solution. The STRIVERDI RESPIMAT inhaler has a yellow-colored cap.

When used with the STRIVERDI RESPIMAT inhaler, each cartridge containing a minimum of 4 grams of a sterile aqueous solution delivers the labeled number of metered actuations after preparation for use. Each dose (one dose equals two actuations) from the STRIVERDI RESPIMAT inhaler delivers 5 mcg olodaterol (equivalent to 5.473 mcg olodaterol hydrochloride) in 22.1 mcL of solution from the mouthpiece. As with all inhaled drugs, the actual amount of drug delivered to the lung may depend on patient factors, such as the coordination between the actuation of the inhaler and inspiration through the delivery system. The duration of inspiration should be at least as long as the spray duration (1.5 seconds).

Prior to first use, the STRIVERDI RESPIMAT cartridge is inserted into the STRIVERDI RESPIMAT inhaler and the unit is primed. When using for the first time, patients are to actuate the inhaler toward the ground until an aerosol cloud is visible and then repeat the process three more times. The unit is then considered primed and ready for use. If not used for more than 3 days, patients are to actuate the inhaler once to prepare the inhaler for use. If not used for more than 21 days, patients are to actuate the inhaler until an aerosol cloud is visible and then repeat the process three more times to prepare the inhaler for use [see Patient Counseling Information (17)].

12 CLINICAL PHARMACOLOGY

12.1 Mechanism of Action

Olodaterol is a long-acting beta2-adrenergic agonist (LABA). The compound exerts its pharmacological effects by binding and activation of beta2-adrenoceptors after topical administration by inhalation. Activation of these receptors in the airways results in a stimulation of intracellular adenyl cyclase, an enzyme that mediates the synthesis of cyclic-3', 5' adenosine monophosphate (cAMP). Elevated levels of cAMP induce bronchodilation by relaxation of airway smooth muscle cells. In vitro studies have shown that olodaterol has 241-fold greater agonist activity at beta2-adrenoceptors compared to beta1-adrenoceptors and 2,299-fold greater agonist activity compared to beta3-adrenoceptors. The clinical significance of these findings is unknown.

Beta-adrenoceptors are divided into three subtypes: beta1-adrenoceptors predominantly expressed on cardiac smooth muscle, beta2-adrenoceptors predominantly expressed on airway smooth muscle, and beta3-adrenoceptors predominantly expressed on adipose tissue. Beta2-agonists cause bronchodilation. Although the beta2-adrenoceptor is the predominant adrenergic receptor in the airway smooth muscle, it is also present on the surface of a variety of other cells, including lung epithelial and endothelial cells and in the heart. The precise function of beta2-receptors in the heart is not known, but their presence raises the possibility that even highly selective beta2-agonists may have cardiac effects.

12.2 Pharmacodynamics

Systemic Safety

The major adverse effects of inhaled beta2-adrenergic agonists occur as a result of excessive activation of systemic beta-adrenergic receptors. The most common adverse effects in adults include skeletal muscle tremor and cramps, insomnia, tachycardia, decreases in serum potassium, and increases in plasma glucose.

Changes in serum potassium were evaluated in COPD patients in double-blind phase 3 studies. In pooled data, at the recommended 5 mcg dose there was no clinically relevant change compared to placebo in serum potassium.

Cardiac Electrophysiology

The effect of STRIVERDI RESPIMAT on the QT/QTc interval of the ECG was investigated in 24 healthy male and female volunteers in a double-blind, randomized, placebo- and active (moxifloxacin)- controlled study at single doses of 10, 20, 30, and 50 mcg. Dose-dependent QTcI (individual subject corrected QT interval) prolongation was observed. The maximum mean (one-sided 95% upper confidence bound) difference in QTcI from placebo after baseline correction was 2.5 (5.6) ms, 6.1 (9.2) ms, 7.5 (10.7) ms and 8.5 (11.6) ms following doses of 10, 20, 30 and 50 mcg, respectively.

The effect of 5 mcg and 10 mcg STRIVERDI RESPIMAT on heart rate and rhythm was assessed using continuous 24-hour ECG recording (Holter monitoring) in a subset of 772 patients in the 48-week, placebo-controlled phase 3 trials. There were no dose- or time-related trends or patterns observed for the magnitudes of mean changes in heart rate or premature beats. Shifts from baseline to the end of treatment in premature beats did not indicate meaningful differences between STRIVERDI RESPIMAT 5 mcg, 10 mcg, and placebo.

12.3 Pharmacokinetics

Olodaterol showed linear pharmacokinetics. On repeated once-daily inhalation steady-state of olodaterol plasma concentrations was achieved after 8 days, and the extent of exposure was increased up to 1.8-fold as compared to a single dose.

Absorption

Olodaterol reaches maximum plasma concentrations generally within 10 to 20 minutes following drug inhalation. In healthy volunteers, the absolute bioavailability of olodaterol following inhalation was estimated to be approximately 30%, whereas the absolute bioavailability was below 1% when given as an oral solution. Thus, the systemic availability of olodaterol after inhalation is mainly determined by lung absorption, while any swallowed portion of the dose only negligibly contributes to systemic exposure.

Distribution

Olodaterol exhibits multi-compartmental disposition kinetics after inhalation as well as after intravenous administration. The volume of distribution is high (1,110 L), suggesting extensive distribution into tissue. In vitro binding of [^14C] olodaterol to human plasma proteins is independent of concentration and is approximately 60%.

Elimination

Total clearance of olodaterol in healthy volunteers is 872 mL/min, and renal clearance is 173 mL/min. The terminal half-life following intravenous administration is 22 hours. The terminal half-life following inhalation in contrast is about 45 hours, indicating that the latter is determined by absorption rather than by elimination processes. However, the effective half-life at daily dose of 5 mcg calculated from Cmax from COPD patients is 7.5 hours.

Metabolism

Olodaterol is substantially metabolized by direct glucuronidation and by O-demethylation at the methoxy moiety followed by conjugation. Of the six metabolites identified, only the unconjugated demethylation product binds to beta2-receptors. This metabolite, however, is not detectable in plasma after chronic inhalation of the recommended therapeutic dose.

Cytochrome P450 isozymes CYP2C9 and CYP2C8, with negligible contribution of CYP3A4, are involved in the O-demethylation of olodaterol, while uridine diphosphate glycosyl transferase isoforms UGT2B7, UGT1A1, 1A7, and 1A9 were shown to be involved in the formation of olodaterol glucuronides.

Excretion

Following intravenous administration of [^14C]-labeled olodaterol, 38% of the radioactive dose was recovered in the urine and 53% was recovered in feces. The amount of unchanged olodaterol recovered in the urine after intravenous administration was 19%. Following oral administration, only 9% of olodaterol and/or its metabolites was recovered in urine, while the major portion was recovered in feces (84%). More than 90% of the dose was excreted within 6 and 5 days following intravenous and oral administration, respectively. Following inhalation, excretion of unchanged olodaterol in urine within the dosing interval in healthy volunteers at steady state accounted for 5% to 7% of the dose.

Specific Populations

A pharmacokinetic meta-analysis showed that no dose adjustment is necessary based on the effect of age, gender, and weight on systemic exposure in COPD patients after inhalation of STRIVERDI RESPIMAT.

Patients with Renal Impairment

Olodaterol levels were increased by approximately 40% in subjects with severe renal impairment. A study in subjects with mild and moderate renal impairment was not performed.

Patients with Hepatic Impairment

Subjects with mild and moderate hepatic impairment showed no changes in Cmax or AUC, nor did protein binding differ between mild and moderate hepatically impaired subjects and their healthy controls. A study in subjects with severe hepatic impairment was not performed.

Drug Interaction Studies

Drug interaction studies were carried out using fluconazole as a model inhibitor of CYP 2C9 and ketoconazole as a potent P-gp (and CYP3A4, 2C8, 2C9) inhibitor.

Fluconazole: Co-administration of 400 mg fluconazole once a day for 14 days had no relevant effect on systemic exposure to olodaterol.

Ketoconazole: Co-administration of 400 mg ketoconazole once a day for 14 days increased olodaterol Cmax by 66% and AUC0-1 by 68%.

Tiotropium: Co-administration of tiotropium bromide, delivered as fixed-dose combination with olodaterol, for 21 days had no relevant effect on systemic exposure to olodaterol, and vice versa.

13 NONCLINICAL TOXICOLOGY

13.1 Carcinogenesis, Mutagenesis, Impairment of Fertility

Two-year inhalation studies were conducted in rats and mice to assess the carcinogenic potential of olodaterol. Lifetime treatment of female rats induced leiomyomas of the mesovarium at doses of 25.8 and 270 mcg/kg/day (approximately 18- and 198-fold, respectively, the MRHDID on an AUC basis). No tumor findings were observed in male rats at doses up to 270 mcg/kg/day (approximately 230-fold the MRHDID on an AUC basis). Lifetime treatment of female mice induced leiomyomas and leiomyosarcomas of the uterus at doses ≥76.9 mcg/kg/day (approximately 106-fold the MRHDID on an AUC basis). No tumor findings were observed in male mice at doses up to 255 mcg/kg/day (approximately 455-fold the MRHDID on an AUC basis). Increases in leiomyomas and leiomyosarcomas of the female rodent reproductive tract have been similarly demonstrated with other β2-adrenergic agonist drugs. The relevance of these findings to human use is unknown.

Olodaterol was not mutagenic in the in vitro Ames test or in the in vitro mouse lymphoma assay. Olodaterol produced increased frequency of micronuclei in rats after intravenous doses. The increased frequency of micronuclei was likely related to drug enhanced (compensatory) erythropoiesis. The mechanism for induction of micronuclei formation is likely not relevant at clinical exposures.

Olodaterol did not impair male or female fertility in rats at inhalation doses up to 3,068 mcg/kg/day (approximately 2,322 times the MRHDID on an AUC basis).

14 CLINICAL STUDIES

The STRIVERDI RESPIMAT clinical development program included three dose-ranging trials in COPD patients, four dose-ranging trials in asthma patients, and eight confirmatory trials in patients with COPD.

Dose-ranging trials

The first COPD dose-ranging trial was a randomized, double-blind, placebo-controlled, single-dose, 5-way cross-over trial in 36 patients. Results demonstrated dose-related improvements in forced expiratory volume in one second (FEV1) compared to placebo. The difference in trough FEV1 from placebo for the 2, 5, 10, and 20 mcg doses were 0.07L (95% CI 0.03, 0.11), 0.10L (0.06, 0.14), 0.11L (0.07, 0.15), and 0.12L (0.08, 0.16), respectively. The second COPD dose-ranging trial was a 4-week, randomized, double-blind, placebo-controlled, parallel group trial in 405 patients. Dose-related improvements in lung function were also seen, with no added benefit of the 20 mcg dose over the 10 mcg dose (Figure 1). The third COPD dose-ranging trial was a randomized, double-blind, 4-way cross-over, dose-regimen trial in 47 patients. Treatment arms included 2 mcg twice-daily, 5 mcg once-daily, 5 mcg twice-daily, and 10 mcg once-daily. There was no clear difference in treatment effect when comparing twice-daily dosing to once-daily dosing.

Figure 1 Difference from placebo for STRIVERDI RESPIMAT for FEV1 AUC0-3hr and trough FEV1 after 4 weeks

Four randomized, double-blind, placebo-controlled dose-ranging trials were performed in patients with asthma, evaluating doses from 2 to 20 mcg. Results from patients with asthma were consistent with results from dose-ranging trials in patients with COPD. STRIVERDI RESPIMAT is not indicated for asthma.

Based upon the results of the dose-ranging trials, 5 and 10 mcg doses were further evaluated in the confirmatory COPD trials.

Confirmatory Trials

The eight confirmatory trials in the STRIVERDI RESPIMAT clinical development program were four pairs of replicate, randomized, double-blind, placebo-controlled trials in 3,533 COPD patients (1,281 received the 5 mcg dose, 1,284 received the 10 mcg dose):

(i) two replicate, placebo-controlled, parallel group, 48 week trials (Trials 1 and 2)
(ii) two replicate, placebo- and active- [formoterol 12 mcg twice-daily] controlled, parallel group, 48-week trials (Trials 3 and 4)
(iii) two replicate, placebo- and active- [formoterol 12 mcg twice-daily] controlled, 6-week cross-over trials (Trials 5 and 6)
(iv) two replicate, placebo- and active- [tiotropium bromide 18 mcg once-daily] controlled, 6-week cross-over trials (Trials 7 and 8).

These eight trials enrolled patients who were 40 years of age or older with a clinical diagnosis of COPD, a smoking history of at least 10 pack-years, and moderate to very severe pulmonary impairment (post-bronchodilator FEV1 less than 80% predicted normal [GOLD II – IV] and a post-bronchodilator FEV1 to FVC ratio of less than 70%).

The majority of the 3,104 patients in the 48-week trials (Trials 1 and 2, Trials 3 and 4) were male (77%), white (66%) or Asian (32%), with a mean age of 64 years. Mean post-bronchodilator FEV1 was 1.38 L (GOLD II [50%], GOLD III [40%], GOLD IV [10%]). Mean beta2-agonist responsiveness was 15% of baseline (0.16 L). With the exception of other LABAs, all pulmonary medications were allowed as concomitant therapy (e.g., tiotropium [24%], ipratropium [25%], inhaled corticosteroids [45%], xanthines [16%]); patient enrollment was stratified by tiotropium use. In all four trials, the primary efficacy endpoints were change from pre-treatment baseline in FEV1 AUC0-3 and trough (pre-dose) FEV1 (after 12 weeks in Trials 1 and 2; after 24 weeks in Trials 3 and 4).

In all four 48-week trials, STRIVERDI RESPIMAT 5 mcg demonstrated significant improvements in FEV1 AUC 0-3hr compared to placebo at week 12 (Table 2) and at week 24. In the four 48-week trials, STRIVERDI RESPIMAT 5 mcg demonstrated significant improvements in trough FEV1 compared to placebo at week 12 (Table 2; 3 of 4 trials) and at week 24 (4 trials). STRIVERDI RESPIMAT 5 mcg demonstrated a bronchodilatory treatment effect at 5 minutes after the first dose with a mean increase in FEV1 compared to placebo of 0.11L (range: 0.10L to 0.12L). The 10 mcg dose demonstrated no additional benefit over the 5 mcg dose (data not shown). Patients treated with STRIVERDI RESPIMAT 5 mcg used less rescue albuterol compared to patients treated with placebo.

Table 2 Differences from placebo for STRIVERDI RESPIMAT 5 mcg for FEV1 AUC0-3hr and trough FEV1 at week 12
 | Difference from placebo [L] (95% CI)
 | FEV1 AUC0-3hr | Trough FEV1
Trial 1 | 0.16 (0.12, 0.21) | 0.08 (0.04, 0.13)
Trial 2 | 0.13 (0.09, 0.18) | 0.03 (-0.01, 0.08)
Trial 3 | 0.18 (0.14, 0.22) | 0.08 (0.04, 0.12)
Trial 4 | 0.15 (0.11, 0.18) | 0.06 (0.02, 0.10)

In Trials 1 and 2, serial spirometric evaluations were performed pre-dose and up to 12 hours after dosing in a sub-group of 562 patients (201 patients receiving STRIVERDI RESPIMAT 5 mcg, 192 patients receiving 10 mcg, and 169 patients receiving placebo) after 12 weeks of treatment. Dosing occurred at approximately the same time of the day in the morning. The spirometric curves from Trial 1 are displayed in Figure 2.

Figure 2 FEV1 profile for STRIVERDI RESPIMAT 5 mcg and placebo at week 12 (pre-dose and up to 12 hrs post-dose) (Trial 1)

The bronchodilatory profile of STRIVERDI RESPIMAT 5 mcg over the 24 hour dosing interval was evaluated in two pairs of replicate, placebo- and active-controlled, 6 week cross-over trials in 199 patients (Trials 5 and 6) and 230 patients (Trials 7 and 8) with moderate to very severe COPD. Mean beta2-agonist responsiveness ranged from 14% -21% of baseline (0.18 to 0.22 L). All pulmonary medications were allowed as concomitant therapy with the exception of other LABAs (all trials) and anti-cholinergics (Trials 7 and 8). In all four trials, the primary endpoints were change from pre-treatment baseline in FEV1 AUC0-12hr and FEV1 AUC12-24hr after 6 weeks; although not a primary endpoint, trough FEV1 was also measured after 6 weeks. Results are shown in Table 3.

Table 3 Differences from placebo for STRIVERDI RESPIMAT 5 mcg after 6 weeks in cross-over spirometry trials
Difference from placebo [L] (95% CI)
 | FEV1 AUC0-12hr | FEV1 AUC12-24hr | Trough FEV1
Trial 5 | 0.15 (0.11, 0.18) | 0.11 (0.07, 0.15) | 0.11 (0.06, 0.15)
Trial 6 | 0.17 (0.14, 0.21) | 0.12 (0.08, 0.15) | 0.10 (0.05, 0.15)
Trial 7 | 0.19 (0.15, 0.23) | 0.13 (0.09, 0.17) | 0.13 (0.10, 0.17)
Trial 8 | 0.20 (0.16, 0.23) | 0.15 (0.12, 0.19) | 0.13 (0.10, 0.17)

16 HOW SUPPLIED/STORAGE AND HANDLING

STRIVERDI RESPIMAT Inhalation Spray is supplied in a labeled carton containing one STRIVERDI RESPIMAT cartridge and one STRIVERDI RESPIMAT inhaler.

The STRIVERDI RESPIMAT cartridge is an aluminum cylinder with a tamper protection seal on the cap. The STRIVERDI RESPIMAT cartridge is only intended for use with the STRIVERDI RESPIMAT inhaler.

The STRIVERDI RESPIMAT inhaler is a cylindrical-shaped plastic inhalation device with a gray-colored body and a clear base. The clear base is removed to insert the cartridge. The inhaler contains a dose indicator. The yellow colored cap and the written information on the label of the gray inhaler body indicates that it is labeled for use with the STRIVERDI RESPIMAT cartridge.

STRIVERDI RESPIMAT Inhalation Spray is available as:

STRIVERDI RESPIMAT Inhalation Spray: 60 metered actuations (NDC 0597-0192-61)

The STRIVERDI RESPIMAT cartridge has a net fill weight of at least 4 grams and when used with the STRIVERDI RESPIMAT inhaler, is designed to deliver the labeled number of metered actuations after preparation for use.

When the labeled number of metered actuations has been dispensed from the inhaler, the STRIVERDI RESPIMAT locking mechanism will be engaged and no more actuations can be dispensed.

After assembly, the STRIVERDI RESPIMAT inhaler should be discarded at the latest 3 months after first use or when the locking mechanism is engaged, whichever comes first.

Keep out of reach of children. Do not spray into eyes.

Storage

Store at 20°C to 25°C (68°F to 77°F); excursions permitted to 15°C to 30°C (59°F to 86°F) [see USP Controlled Room Temperature]. Avoid freezing.

17 PATIENT COUNSELING INFORMATION

Advise the patient to read the FDA-approved patient labeling (Patient Information and Instructions for Use).

Serious Asthma-Related Events

Inform patients that LABA, such as STRIVERDI RESPIMAT, when used as monotherapy [without an inhaled corticosteroid], increase the risk of serious asthma-related events, including asthma-related death. STRIVERDI RESPIMAT is not indicated for the treatment of asthma.

Not for Acute Symptoms

STRIVERDI RESPIMAT is not meant to relieve acute asthma symptoms or exacerbations of COPD and extra doses should not be used for that purpose. Acute symptoms should be treated with an inhaled, short-acting beta2-agonist such as albuterol. (The healthcare provider should provide the patient with such medication and instruct the patient in how it should be used.)

Instruct patients to notify their physician immediately if they experience any of the following:

- Worsening of symptoms
- Decreasing effectiveness of inhaled, short-acting beta2-agonists
- Need for more inhalations than usual of inhaled, short-acting beta2-agonists
- Significant decrease in lung function as outlined by the physician

Instruct patients not to stop therapy with STRIVERDI RESPIMAT without physician/provider guidance since symptoms may recur after discontinuation.

Do Not Use Additional Long-Acting Beta2-Agonists

Patients who have been taking inhaled, short-acting beta2-agonists on a regular basis should be instructed to discontinue the regular use of these products and use them only for the symptomatic relief of acute symptoms.

When patients are prescribed STRIVERDI RESPIMAT, other inhaled medications containing long-acting beta2-agonists should not be used. Patients should not use more than the recommended once-daily dosage of STRIVERDI RESPIMAT. Excessive use of sympathomimetics may cause significant cardiovascular effects, and may be fatal.

Risks Associated with Beta2-Agonist Therapy

Inform patients of adverse effects associated with beta2-agonists, such as palpitations, chest pain, rapid heart rate, tremor, or nervousness.

Paradoxical Bronchospasm

Inform patients that STRIVERDI RESPIMAT can produce paradoxical bronchospasm. Advise patients that if paradoxical bronchospasm occurs, patients should discontinue STRIVERDI RESPIMAT.

Hypersensitivity Reactions

Inform patients that immediate hypersensitivity reactions, including angioedema, may occur after administration of STRIVERDI RESPIMAT. Advise patient to immediately discontinue STRIVERDI RESPIMAT and consult a physician.

Instructions for Administering STRIVERDI RESPIMAT

It is important for patients to understand how to correctly administer STRIVERDI RESPIMAT inhalation spray using the STRIVERDI RESPIMAT inhaler. Instruct patients that STRIVERDI RESPIMAT inhalation spray should only be administered via the STRIVERDI RESPIMAT inhaler and the STRIVERDI RESPIMAT inhaler should not be used for administering other medications.

Instruct patients that priming STRIVERDI RESPIMAT is essential to ensure appropriate content of the medication in each actuation.

When using the unit for the first time, the STRIVERDI RESPIMAT cartridge is inserted into the STRIVERDI RESPIMAT inhaler and the unit is primed. STRIVERDI RESPIMAT patients are to actuate the inhaler toward the ground until an aerosol cloud is visible and then repeat the process three more times. The unit is then considered primed and ready for use. If not used for more than 3 days, patients are to actuate the inhaler once to prepare the inhaler for use. If not used for more than 21 days, patients are to actuate the inhaler until an aerosol cloud is visible and then repeat the process three more times to prepare the inhaler for use.

Distributed by:
Boehringer Ingelheim Pharmaceuticals, Inc.
Ridgefield, CT 06877 USA

Licensed from:
Boehringer Ingelheim International GmbH

STRIVERDI® and RESPIMAT® are registered trademarks of and are used under license from Boehringer Ingelheim International GmbH

Copyright © 2025 Boehringer Ingelheim International GmbH
ALL RIGHTS RESERVED

COL10540BA022025
SPL10542C

PATIENT INFORMATION
STRIVERDI® RESPIMAT® (STRIH ver dee– RES peh mat)
(olodaterol inhalation spray), for oral inhalation use

What is STRIVERDI RESPIMAT?

- STRIVERDI RESPIMAT is a long-acting beta2-adrenergic agonist (LABA) medicine, olodaterol.
- LABA medicines such as STRIVERDI RESPIMAT help the muscles around the airways in your lungs stay relaxed to prevent symptoms, such as wheezing, cough, chest tightness, and shortness of breath. These symptoms can happen when the muscles around the airways tighten. This makes it hard to breathe.
- STRIVERDI RESPIMAT is for long-term use and should be taken as 2 puffs 1 time each day to improve the symptoms of COPD for better breathing.
- STRIVERDI RESPIMAT is a prescription medicine used to control the symptoms of COPD in adults with COPD. COPD is a chronic lung disease that includes chronic bronchitis, emphysema, or both.
- STRIVERDI RESPIMAT is not used to treat sudden symptoms of COPD. Always have a beta2-agonist inhaler medicine (rescue inhaler) with you to treat sudden symptoms of COPD. If you do not have a rescue inhaler medicine, contact your healthcare provider to have one prescribed for you.
- STRIVERDI RESPIMAT is not for the treatment of asthma. It is not known if STRIVERDI RESPIMAT is safe and effective in people with asthma.
- STRIVERDI RESPIMAT should not be used in children. It is not known if STRIVERDI RESPIMAT is safe and effective in children.

Do not use STRIVERDI RESPIMAT if you have asthma.

Before you use STRIVERDI RESPIMAT, tell your healthcare provider about all of your medical conditions, including if you:

- have heart problems.
- have high blood pressure.
- have seizures.
- have thyroid problems.
- have diabetes.
- are pregnant or plan to become pregnant. It is not known if the medicine olodaterol in STRIVERDI RESPIMAT can harm your unborn baby.
- are breastfeeding or plan to breastfeed. It is not known if the medicine olodaterol in STRIVERDI RESPIMAT passes into your breast milk and if it can harm your baby. You and your healthcare provider should decide if you will take STRIVERDI RESPIMAT while breastfeeding.
- are allergic to any of the ingredients in STRIVERDI RESPIMAT, any other medicines, or food products.

Tell your healthcare provider about all the medicines you take, including prescription and over-the-counter medicines, vitamins, and herbal supplements. STRIVERDI RESPIMAT and certain other medicines may affect each other. This may cause serious side effects.
Know the medicines you take. Keep a list of your medicines with you to show your healthcare provider and pharmacist each time you get a new medicine.

How should I use STRIVERDI RESPIMAT?
Read the step-by-step instructions for using STRIVERDI RESPIMAT at the end of this Patient Information leaflet.

- Do not use STRIVERDI RESPIMAT unless your healthcare provider has taught you how to use the inhaler and you understand how to use it correctly. Ask your healthcare provider or pharmacist if you have any questions.
- The STRIVERDI RESPIMAT inhaler has a slow-moving mist that helps you inhale the medicine.
- Use STRIVERDI RESPIMAT exactly as your healthcare provider tells you to use it. Do not use STRIVERDI RESPIMAT more often than prescribed.
- Use 1 dose (2 puffs) of STRIVERDI RESPIMAT, 1 time each day, at the same time of the day.
- If you miss a dose of STRIVERDI RESPIMAT, take it as soon as you remember. Do not take more than 1 dose (2 puffs) in 24 hours.
- If you take too much STRIVERDI RESPIMAT, call your healthcare provider or go to the nearest hospital emergency room right away.
- Do not spray STRIVERDI RESPIMAT in your eyes.
- STRIVERDI RESPIMAT Inhalation Spray should only be given using the STRIVERDI RESPIMAT inhaler. The STRIVERDI RESPIMAT inhaler should not be used to give other medicines.
- Always use the new STRIVERDI RESPIMAT inhaler that is provided with each new prescription.
- STRIVERDI RESPIMAT does not relieve sudden symptoms of COPD. You should not take extra doses of STRIVERDI RESPIMAT to relieve sudden symptoms of COPD. Always have a rescue inhaler medicine with you to treat sudden symptoms. If you do not have a rescue inhaler medicine, call your healthcare provider to have one prescribed for you.
- Do not stop using STRIVERDI RESPIMAT or other medicines to control or treat your COPD unless told to do so by your healthcare provider because your symptoms might get worse. Your healthcare provider will change your medicines as needed.
- If your COPD symptoms worsen over time do not increase your dose of STRIVERDI RESPIMAT, instead call your healthcare provider.
- Do not use STRIVERDI RESPIMAT:
  - more often than prescribed for you,
  - at a higher dose than prescribed for you, or
  - with other LABA medicines. Ask your healthcare provider or pharmacist if any of your other medicines are LABA medicines.
- Call your healthcare provider or get emergency medical care right away if your breathing problems worsen with STRIVERDI RESPIMAT, you need to use your rescue inhaler medicine more often than usual, or your rescue inhaler medicine does not work as well for you at relieving your symptoms.

What are the possible side effects of STRIVERDI RESPIMAT?
STRIVERDI RESPIMAT can cause serious side effects, including:

- serious problems from asthma. People with asthma who take long-acting beta2-adrenergic agonist (LABA) medicines, such as STRIVERDI RESPIMAT, without also using a medicine called an inhaled corticosteroid, have an increased risk of serious problems from asthma, including being hospitalized, needing a tube placed in their airway to help them breathe, or death.
- call your healthcare provider if breathing problems worsen over time while using STRIVERDI RESPIMAT. You may need a different treatment.
  Get emergency medical care if:
  - your breathing problems worsen quickly
  - you use your rescue inhaler medicine, but it does not relieve your breathing problems.

- using too much of a LABA medicine may cause:

- chest pain
- fast and irregular heartbeat
- tremor

- increased blood pressure
- headache
- nervousness

- COPD symptoms can get worse over time. If your COPD symptoms worsen over time, do not increase your dose of STRIVERDI RESPIMAT, instead call your healthcare provider.
- sudden shortness of breath can happen immediately after using STRIVERDI RESPIMAT. Sudden shortness of breath may be life-threatening. Stop taking STRIVERDI RESPIMAT and call your healthcare provider or get emergency medical help right away if you get sudden shortness of breath after using STRIVERDI RESPIMAT.
- effects on your heart, including fast or irregular heartbeat, palpitations, chest pain or increased blood pressure.
- changes in laboratory blood levels including high blood sugar (hyperglycemia) and low levels of potassium (hypokalemia), which may cause symptoms of muscle weakness or abnormal heart rhythm.
- serious allergic reactions including rash, hives, itching, swelling of the face, lips, tongue, throat, difficulties in breathing or swallowing. Stop taking STRIVERDI RESPIMAT and get emergency medical help right away if you get any symptoms of a serious allergic reaction after using STRIVERDI RESPIMAT.

Common side effects of STRIVERDI RESPIMAT include: runny nose, sore throat, upper respiratory infection, bronchitis, urinary tract infection, cough, dizziness, rash, diarrhea, back pain, and joint pain.
These are not all the side effects of STRIVERDI RESPIMAT. Call your doctor for medical advice about side effects. You may report side effects to FDA at 1-800-FDA-1088.

How should I store STRIVERDI RESPIMAT?

- Store STRIVERDI RESPIMAT at room temperature, between 68°F to 77°F (20°C to 25°C).
- Do not freeze your STRIVERDI cartridge or RESPIMAT inhaler.
- Keep STRIVERDI RESPIMAT inhaler, cartridge, and all medicines out of the reach of children.

General information about safe and effective use of STRIVERDI RESPIMAT.
Medicines are sometimes prescribed for purposes other than those listed in a Patient Information leaflet. Do not use STRIVERDI RESPIMAT for a condition for which it was not prescribed. Do not give STRIVERDI RESPIMAT to other people, even if they have the same symptoms that you have. It may harm them.
You can ask your healthcare provider or pharmacist for information about STRIVERDI RESPIMAT that is written for health professionals.

Active ingredient: olodaterol
Inactive ingredients: anhydrous citric acid, benzalkonium chloride, edetate disodium, and water for injection
Distributed by:
Boehringer Ingelheim Pharmaceuticals, Inc.
Ridgefield, CT 06877 USA
Licensed from:
Boehringer Ingelheim International GmbH
STRIVERDI® and RESPIMAT® are registered trademarks of and are used under license from Boehringer Ingelheim International GmbH
Copyright © 2025 Boehringer Ingelheim International GmbH
ALL RIGHTS RESERVED
COL10540BA022025
This product's label may have been updated. For current full prescribing information for STRIVERDI RESPIMAT, go to www.STRIVERDI.com or to view a video demonstration on how to use your STRIVERDI RESPIMAT inhaler, scan the code or visit www.themist.com. You may also call 1-800-542-6257 for further information about STRIVERDI RESPIMAT.

This Patient Information has been approved by the U.S. Food and Drug Administration

Revised: 1/2025

Instructions for Use

STRIVERDI® RESPIMAT® (STRIH ver dee- RES peh mat)

(olodaterol inhalation spray), for oral inhalation use

For Oral Inhalation Only

Do not spray STRIVERDI RESPIMAT into your eyes.

Read these Instructions for Use before you start using STRIVERDI RESPIMAT and each time you get a refill. There may be new information. This leaflet does not take the place of talking to your doctor about your medical condition or your treatment.

You will need to use this inhaler 1 time each day, at the same time each day. Each time you use it take 2 puffs.

Do not turn the clear base before inserting the cartridge.

How to store your STRIVERDI RESPIMAT inhaler

- Store STRIVERDI RESPIMAT at room temperature between 68°F to 77°F (20°C to 25°C).
- Do not freeze your STRIVERDI RESPIMAT cartridge and inhaler.
- If STRIVERDI RESPIMAT has not been used for more than 3 days, release 1 puff towards the ground.
- If STRIVERDI RESPIMAT has not been used for more than 21 days, repeat steps 4 to 6 under the "Prepare for first use" until a mist is visible. Then repeat steps 4 to 6 three more times.
- Keep your STRIVERDI RESPIMAT cartridge and inhaler out of the reach of children.

How to care for your STRIVERDI RESPIMAT inhaler

Clean the mouthpiece, including the metal part inside the mouthpiece, with a damp cloth or tissue only, at least once a week. Any minor discoloration in the mouthpiece does not affect your STRIVERDI RESPIMAT inhaler.

When to get a new STRIVERDI RESPIMAT inhaler

- Your inhaler contains 60 puffs (30 doses) if used as indicated (2 puffs once daily). If you have a sample, your inhaler contains 28 puffs (14 doses) if used as indicated (2 puffs once daily).
- The dose indicator shows approximately how much medicine is left.
- When the dose indicator enters the red area of the scale you need to get a refill; there is approximately medicine for 7 days left (if you have a sample, there is approximately medicine for 3 days left).
- When the dose indicator reaches the end of the red scale, your STRIVERDI RESPIMAT is empty and automatically locks. At this point, the clear base cannot be turned any further.
- Three months after insertion of cartridge, throw away the STRIVERDI RESPIMAT even if it has not been used, or when the inhaler is locked, or when it expires, whichever comes first.

Prepare for first use

1. Remove clear base

- Keep the cap closed.
- Press the safety catch while firmly pulling off the clear base with your other hand. Be careful not to touch the piercing element.
- Write the discard by date on the label (3 months from the date the cartridge is inserted).

2. Insert cartridge

- Insert the narrow end of the cartridge into the inhaler.
- Place the inhaler on a firm surface and push down firmly until it clicks into place.

3. Replace clear base

- Put the clear base back into place until it clicks.
- Do not remove the clear base or the cartridge after it has been put together.

4. Turn

- Keep the cap closed.
- Turn the clear base in the direction of the arrows on the label until it clicks (half a turn).

5. Open

- Open the cap until it snaps fully open.

6. Press

- Point the inhaler toward the ground.
- Press the dose-release button.
- Close the cap.
- If you do not see a mist, repeat steps 4 to 6 until a mist is seen.
- After a mist is seen, repeat steps 4 to 6 three more times.
- After complete preparation of your inhaler, it will be ready to deliver the number of puffs on the label.

Daily use (T O P)

Turn

- Keep the cap closed.
- Turn the clear base in the direction of the arrows on the label until it clicks (half a turn).

Open

- Open the cap until it snaps fully open.

Press

- Breathe out slowly and fully.
- Close your lips around the mouthpiece without covering the air vents.
- Point the inhaler to the back of your throat.
- While taking a slow, deep breath through your mouth, Press the dose-release button and continue to breathe in.
- Hold your breath for 10 seconds or for as long as comfortable.
- Repeat Turn, Open, Press (TOP) for a total of 2 puffs.
- Close the cap until you use your inhaler again.

Answers to Common Questions

It is difficult to insert the cartridge deep enough:

Did you accidentally turn the clear base before inserting the cartridge? Open the cap, press the dose-release button, then insert the cartridge.

Did you insert the cartridge with the wide end first? Insert the cartridge with the narrow end first.

I cannot press the dose-release button:

Did you turn the clear base? If not, turn the clear base in a continuous movement until it clicks (half a turn).

Is the dose indicator on the STRIVERDI RESPIMAT pointing to zero? The STRIVERDI RESPIMAT inhaler is locked after 60 puffs (30 doses). If you have a sample, the STRIVERDI RESPIMAT inhaler is locked after 28 puffs (14 doses). Prepare and use your new STRIVERDI RESPIMAT inhaler.

I cannot turn the clear base:

Did you turn the clear base already? If the clear base has already been turned, follow steps "Open" and "Press" under "Daily use" to get your medicine.

Is the dose indicator on the STRIVERDI RESPIMAT pointing to zero? The STRIVERDI RESPIMAT inhaler is locked after 60 puffs (30 doses). If you have a sample, the STRIVERDI RESPIMAT inhaler is locked after 28 puffs (14 doses). Prepare and use your new STRIVERDI RESPIMAT inhaler.

The dose indicator on the STRIVERDI RESPIMAT reaches zero too soon:

Did you use STRIVERDI RESPIMAT as indicated (2 puffs once daily)? STRIVERDI RESPIMAT will deliver 60 puffs and last 30 days if used at 2 puffs once daily. If you have a sample, STRIVERDI RESPIMAT will deliver 28 puffs and last 14 days if used at 2 puffs once daily.

Did you turn the clear base before you inserted the cartridge? The dose indicator counts each turn of the clear base regardless whether a cartridge has been inserted or not.

Did you spray in the air often to check whether the STRIVERDI RESPIMAT is working? Once you have prepared STRIVERDI RESPIMAT, no test-spraying is required if used daily.

Did you insert the cartridge into a used STRIVERDI RESPIMAT? Always insert a new cartridge into a NEW STRIVERDI RESPIMAT.

My STRIVERDI RESPIMAT sprays automatically:

Was the cap open when you turned the clear base? Close the cap, then turn the clear base.

Did you press the dose-release button when turning the clear base? Close the cap, so the dose-release button is covered, then turn the clear base.

Did you stop when turning the clear base before it clicked? Turn the clear base in a continuous movement until it clicks (half a turn).

My STRIVERDI RESPIMAT doesn't spray:

Did you insert a cartridge? If not, insert a cartridge.

Did you repeat Turn, Open, Press (TOP) less than three times after inserting the cartridge? Repeat Turn, Open, Press (TOP) three times after inserting the cartridge as shown in steps 4 to 6 under "Prepare for first use".

Is the dose indicator on the STRIVERDI RESPIMAT pointing to 0? You have used up all your medicine and the inhaler is locked.

This product's label may have been updated. For current full prescribing information for STRIVERDI RESPIMAT, go to www.STRIVERDI.com or to view a video demonstration on how to use your STRIVERDI RESPIMAT inhaler, scan the code or visit www.themist.com. You may also call 1-800-542-6257 for further information about STRIVERDI RESPIMAT.

This Patient Information and Instructions for Use has been approved by the U.S. Food and Drug Administration.

Distributed by: Boehringer Ingelheim Pharmaceuticals, Inc., Ridgefield, CT 06877 USA

Licensed from: Boehringer Ingelheim International GmbH

STRIVERDI® and RESPIMAT® are registered trademarks of and are used under license from Boehringer Ingelheim International GmbH

Copyright © 2025 Boehringer Ingelheim International GmbH
ALL RIGHTS RESERVED

Revised: January 2025

COL10540BA022025

PRINCIPAL DISPLAY PANEL - 2.5 mcg Cartridge Carton

NDC 0597-0192-61
Striverdi® Respimat®
(olodaterol inhalation spray)

2.5 mcg/actuation*

FOR ORAL INHALATION ONLY

ATTENTION PHARMACIST:
Dispense with Instructions for Use

Rx only

4 Grams
60 Metered Inhalations
(Two inhalations equal one dose)

Boehringer
Ingelheim